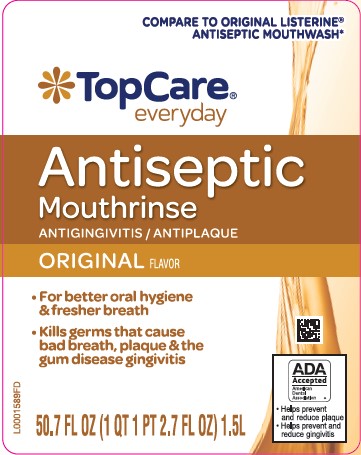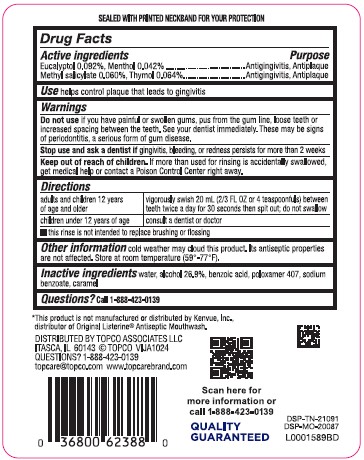 DRUG LABEL: Original Antiseptic
NDC: 36800-318 | Form: MOUTHWASH
Manufacturer: Topco Associates LLC
Category: otc | Type: HUMAN OTC DRUG LABEL
Date: 20260213

ACTIVE INGREDIENTS: EUCALYPTOL 0.92 mg/1 mL; MENTHOL 0.42 mg/1 mL; METHYL SALICYLATE 0.6 mg/1 mL; THYMOL 0.64 mg/1 mL
INACTIVE INGREDIENTS: WATER; ALCOHOL; BENZOIC ACID; POLOXAMER 407; SODIUM BENZOATE; CARAMEL

Top Care 318.003/318AH-AI
Antiseptic Mouthrinse

Tamper Evident Statement

SEALED WITH PRINTED NECKBAND FOR YOUR PROTECTION

Active Ingredients

Eucalyptol 0.092%

Menthol 0.042%

Methyl salicylate 0.060%

Thymol 0.064%

Purpose

Antigingivitis, Antiplaque

Use

helps control plaque that leads to gingivitis

Warnings

for this product

Do Not Use

if you have painful or swollen gums, pus from the gum line, loose teeth or increased spacing between the teeth. See your dentist immediately. These may be signs of periodontitis, a serious form of gum disease.

Stop use and ask a dentist if

gingivitis, bleeding, or redness persists for more than 2 weeks

Keep out of reach of children.

If more than used for rinsing is accidentally swallowed, get medical help or contact a Poison Control Center right away.

Directions

adults and children 12 years of age and older - vigorously swish 20 mL (2/3 FL OZ or 4 teaspoonfuls) between teeth twice a day for 30 seconds then spit out; do not swallow

children under 12 years of age - consult a dentist or doctor

- this rinse is not intended to replace brushing or flossing

Other information

cold weather may cloud this product. Its antiseptic properties are not affected. Store at room temperature (59°-77°F).

Inactive ingredients

water, alcohol 26.9%, benzoic acid, poloxamer 407, sodium benzoate, caramel

Questions?

Call 1-888-423-0139

Disclaimer

*This product is not manufactured or distributed by Johnson & Johnson Healthcare Products, distributor of Original Listerine® Antispetic Mouthwash.

Adverse Reactions

DISTRIBUTED BY: TOPCO ASSOCIATES LLC

ITASCA, IL 60143 ©TOPCO VIJA1024

QUESTIONS? 1-888-423-0139

topcare@topco.com www.topcarebrand.com

Scan here for more information or call 1-888-423-0139

Quality Guaranteed

DSP-TN-21091

DSP-MO-20087

Principal display panel

COMPARE TO ORIGINAL LISTERINE®ANTISEPTIC MOUTHWASH*

TopCare®

everyday

Antiseptic

Mouthrinse

ANTIGINGIVITIS/ANTIPLAQUE

ORIGINAL FLAVOR

- For better oral hygiene & fresher breath
- Kills germs that cause bad breath, plaque & the gum disease gingivitis

ADA Accepted

American Dental Association

- Helps prevent and reduce plaque
- Helps prevent and reduce gingivitis

50.7 FL OZ (1 QT 1 PT 2.7 FL OZ) 1.5 L